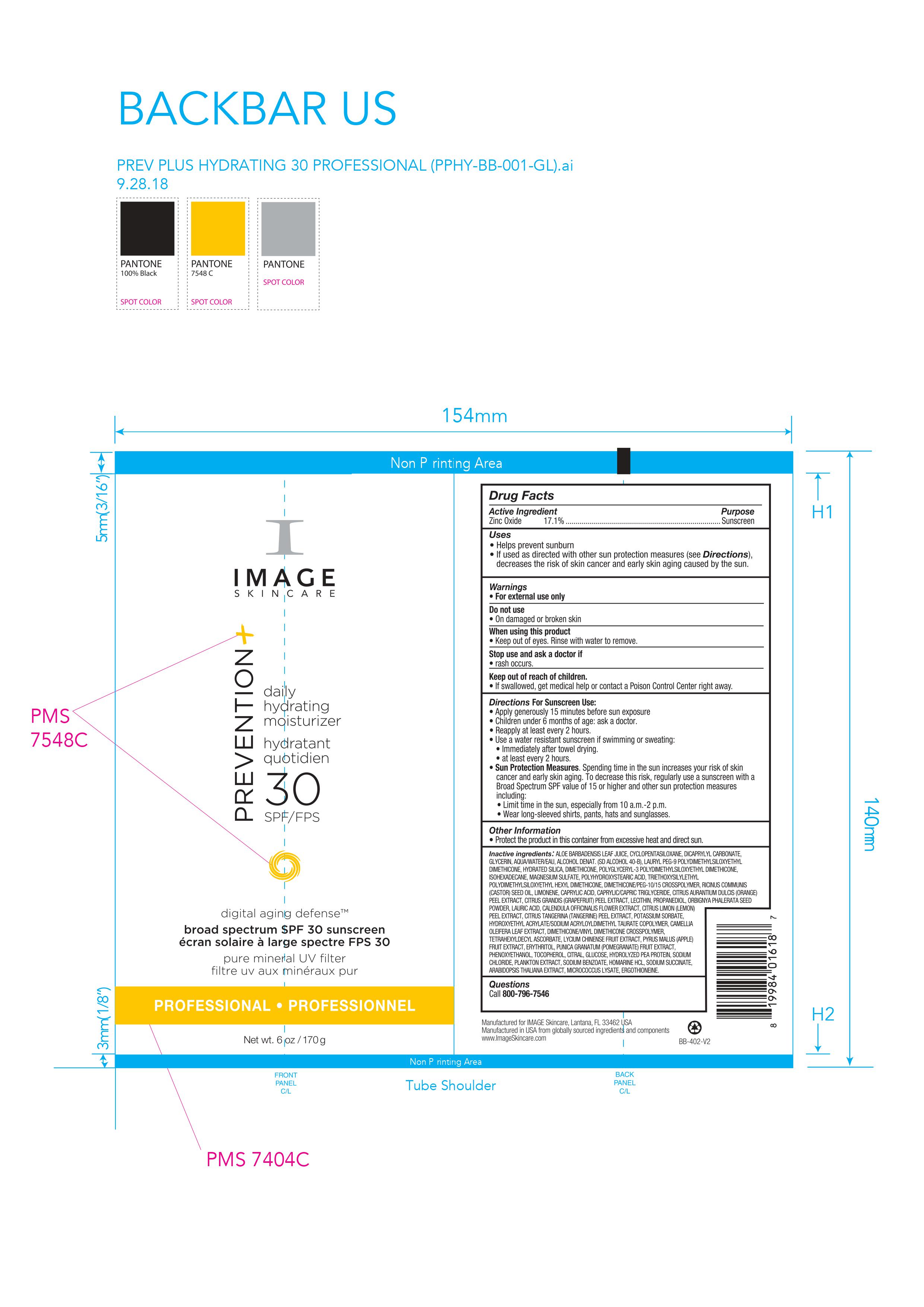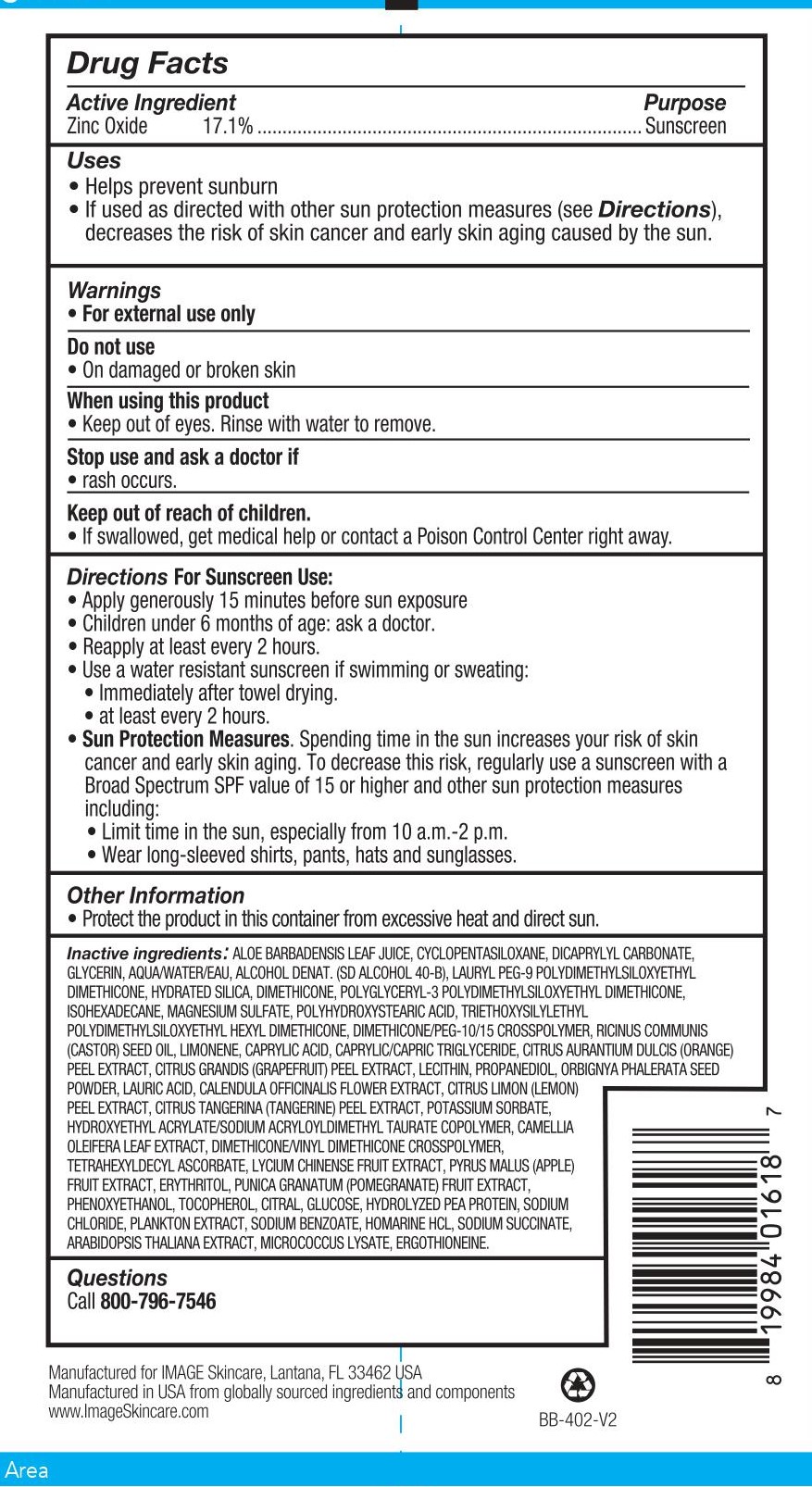 DRUG LABEL: Image Skincare Prevention Plus Daily Hydrating Moisturizer
NDC: 79458-001 | Form: CREAM
Manufacturer: Natural Technology, LLC
Category: otc | Type: HUMAN OTC DRUG LABEL
Date: 20220317

ACTIVE INGREDIENTS: ZINC OXIDE 171 g/1000 g
INACTIVE INGREDIENTS: ALCOHOL; CALENDULA OFFICINALIS FLOWER; POTASSIUM SORBATE; CAMELLIA OLEIFERA LEAF; TRIETHOXYSILYLETHYL POLYDIMETHYLSILOXYETHYL HEXYL DIMETHICONE; HYDRATED SILICA; DIMETHICONE; ARABIDOPSIS THALIANA; CITRUS MAXIMA FRUIT RIND; TANGERINE PEEL; HYDROXYETHYL ACRYLATE/SODIUM ACRYLOYLDIMETHYL TAURATE COPOLYMER (100000 MPA.S AT 1.5%); CAPRYLIC ACID; LECITHIN, SOYBEAN; CYCLOMETHICONE 5; DICAPRYLYL CARBONATE; MICROCOCCUS LUTEUS; ANACYSTIS NIDULANS EXTRACT; WATER; DIMETHICONE/VINYL DIMETHICONE CROSSPOLYMER (SOFT PARTICLE); ORANGE PEEL; TOCOPHEROL; LYCIUM CHINENSE FRUIT; PHENOXYETHANOL; ERGOTHIONEINE; GLYCERIN; APPLE; PEA PROTEIN; CITRAL; ANHYDROUS DEXTROSE; CASTOR OIL; MAGNESIUM SULFATE, UNSPECIFIED; POLYHYDROXYSTEARIC ACID (2300 MW); PROPANEDIOL; TETRAHEXYLDECYL ASCORBATE; ALOE VERA LEAF; LAURIC ACID; LIMONENE, (+)-; LAURYL PEG-9 POLYDIMETHYLSILOXYETHYL DIMETHICONE; LEMON PEEL; SODIUM CHLORIDE; POMEGRANATE; SODIUM BENZOATE; HOMARINE HYDROCHLORIDE; SODIUM SUCCINATE HEXAHYDRATE; POLYGLYCERYL-3 POLYDIMETHYLSILOXYETHYL DIMETHICONE (4000 MPA.S); ISOHEXADECANE; DIMETHICONE/PEG-10/15 CROSSPOLYMER; BABASSU SEED; MEDIUM-CHAIN TRIGLYCERIDES; ERYTHRITOL

Zinc Oxide 17.1%. Purpose: Sunscreen

170g. NDC: 79458-001-00

Purpose: Sunscreen

170g. NDC: 79458-001-00

Helps prevent sunburn. If used as directed with other sun protection measures (see Directions), decreases the risk of skin cancer and early skin aging caused by the sun.

170 g. NDC: 79458-000-07

For external use only

170 g. NDC: 79458-001-00

Do not use on damaged or broken skin.

170 g. NDC: 79458-001-00

When using this product keep out of eyes. Rinse with water to remove.

170 g. NDC: 79458-001-00

Stop use and ask a doctor if rash occurs.

170 g. NDC: 79458-001-00

Keep out of reach of children. If swallowed, get medical help or contact a Poison Control Center right away.

170 g. NDC: 79458-001-00

Apply generously 15 minutes before sun exposure. Children under 6 months of age: ask a doctor. Reapply at least every 2 hours. Use a water resistant sunscreen if swimming or sweating: Immediately after towel drying. At least every 2 hours. Sun Protection Measures. Spending time in the sun increases your risk of skin cancer and early skin aging. To decrease this risk, regularly use a sunscreen with a Broad Spectrum SPF value of 15 or higher and other sun protection measures including: Limit time in the sun, especially from 10am to 2pm. Wear long-sleeved shirts, pants, hats and sunglasses.

170 g. NDC: 79458-001-00

Protect the product in this container from excessive heat and direct sun.

170 g. NDC: 79458-000-07

Aloe Barbadensis Leaf Juice, Cyclopentasiloxane, Dicaprylyl Carbonate, Glycerin, Aqua/Water/Eau, Alcohol Denat. (SD Alcohol 40-B), Lauryl PEG-9 Polydimethylsiloxyethyl Dimethicone, Hydrated Silica, Dimethicone, Polyglyceryl-3 Polydimethylsiloxyethyl Dimethicone, Isohexadecane, Magnesium Sulfate, Polyhydroxystearic Acid, Triethoxysilylethyl Polydimethylsiloxyethyl Hexyl Dimethicone, Dimethicone/PEG-10/15 Crosspolymer, Ricinus Communis (Castor) Seed Oil, Limonene, Caprylic Acid, Caprylic/Capric Triglyceride, Citrus Aurantium Dulcis (Orange) Peel Extract, Citrus Grandis (Grapefruit) Peel Extract, Lecithin, Propanediol, Orbignya Phalerata Seed Powder, Lauric Acid, Calendula Officinalis Flower Extract, Citrus Limon (Lemon) Peel Extract, Citrus Tangerina (Tangerine) Peel Extract, Potassium Sorbate, Hydroxyethyl Acrylate/Sodium Acryloydimethyl Taurate Copolymer, Camellia Oleifera Leaf Extract, Dimethicone/Vinyl Dimethicone Crosspolymer, Tetrahexyldecyl Ascorbate, Lycium Chinense Fruit Extract, Pyrus Malus (Apple) Fruit Extract, Erythritol, Punica Granatum (Pomegranate) Fruit Extract, Phenoxyethanol, Tocopherol, Citral, Glucose, Hydrolyzed Pea Protein, Sodium Chloride, Plankton Extract, Sodium Benzoate, Homarine HCL, Sodium Succinate, Arabidopsis Thaliana Extract, Micrococcus Lysate, Ergothioneine

170 g. NDC: 79458-001-00

Prevention plus daily hydrating moisturizer 30 SPF/FPS

170 g. NDC: 79458-001-00